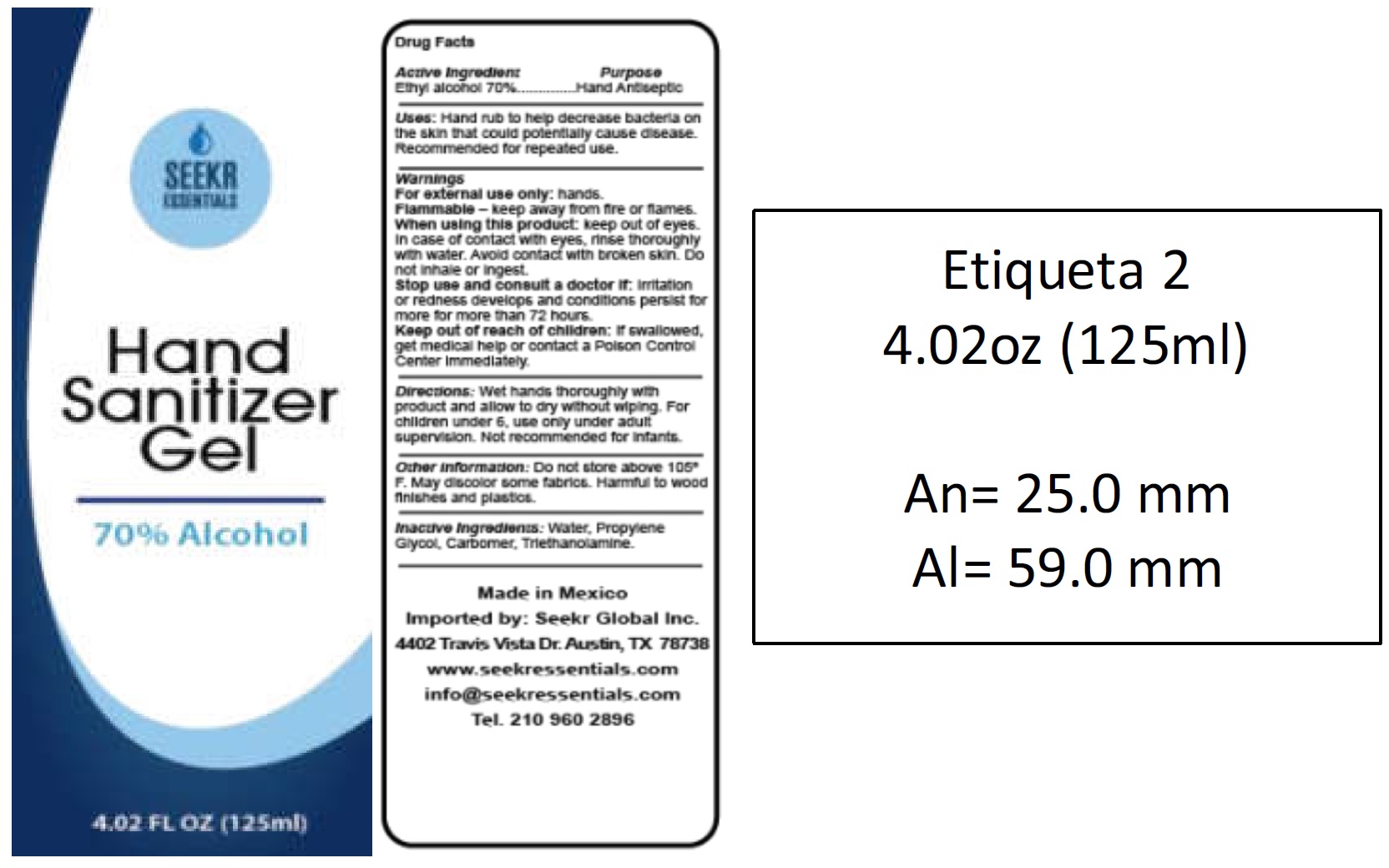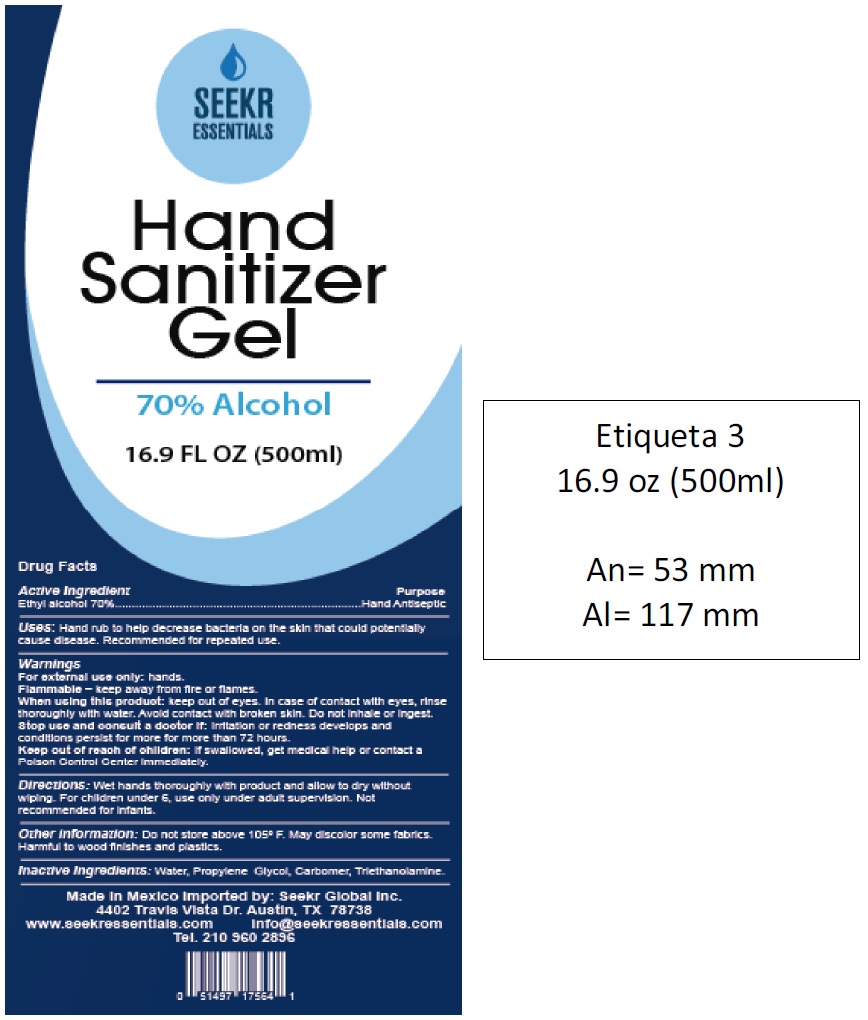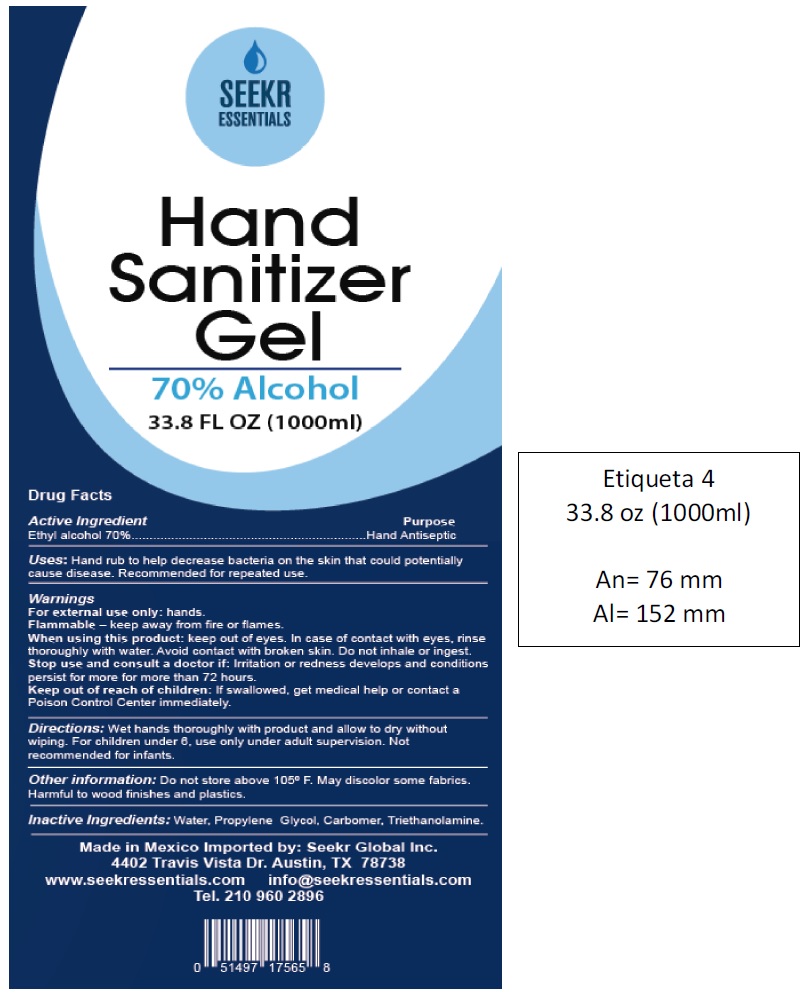 DRUG LABEL: Seekr Essentials Hand Sanitizer
NDC: 79439-001 | Form: GEL
Manufacturer: Seekr Global Inc.
Category: otc | Type: HUMAN OTC DRUG LABEL
Date: 20200715

ACTIVE INGREDIENTS: ALCOHOL 0.7 mL/1 mL
INACTIVE INGREDIENTS: WATER; PROPYLENE GLYCOL; CARBOMER HOMOPOLYMER, UNSPECIFIED TYPE; TROLAMINE

Seekr Essentials Hand Sanitizer

Active Ingredient

Ethyl alcohol 70%

Purpose

Hand Antiseptic

Uses:

Hand rub to help decrease bacteria on the skin that could potentially cause disease. Recommended for repeated use.

Warnings

For external use only: hands.

Flammable - keep away from fire or flames.

When using this product:

keep out of eyes. In case of contact with eyes, rinse thoroughly with water. Avoid contact with broken skin. Do not inhale or ingest.

Stop use and consult a doctor if:

irritation or redness develops and conditions persist for more for more than 72 hours.

Keep out of reach of children:

If swallowed, get medical help or contact a Poison Control Center immediately.

Directions:

Wet hands thoroughly with product and allow to dry without wiping, For children under 6, use only under adult supervision. Not recommended for infants.

Other Information:

Do not store above 105° F. May discolor some fabrics. Harmful to wood finishes and plastics.

Inactive Ingredients:

Water, Propylene Glycol, Carbomer, Triethanolamine.